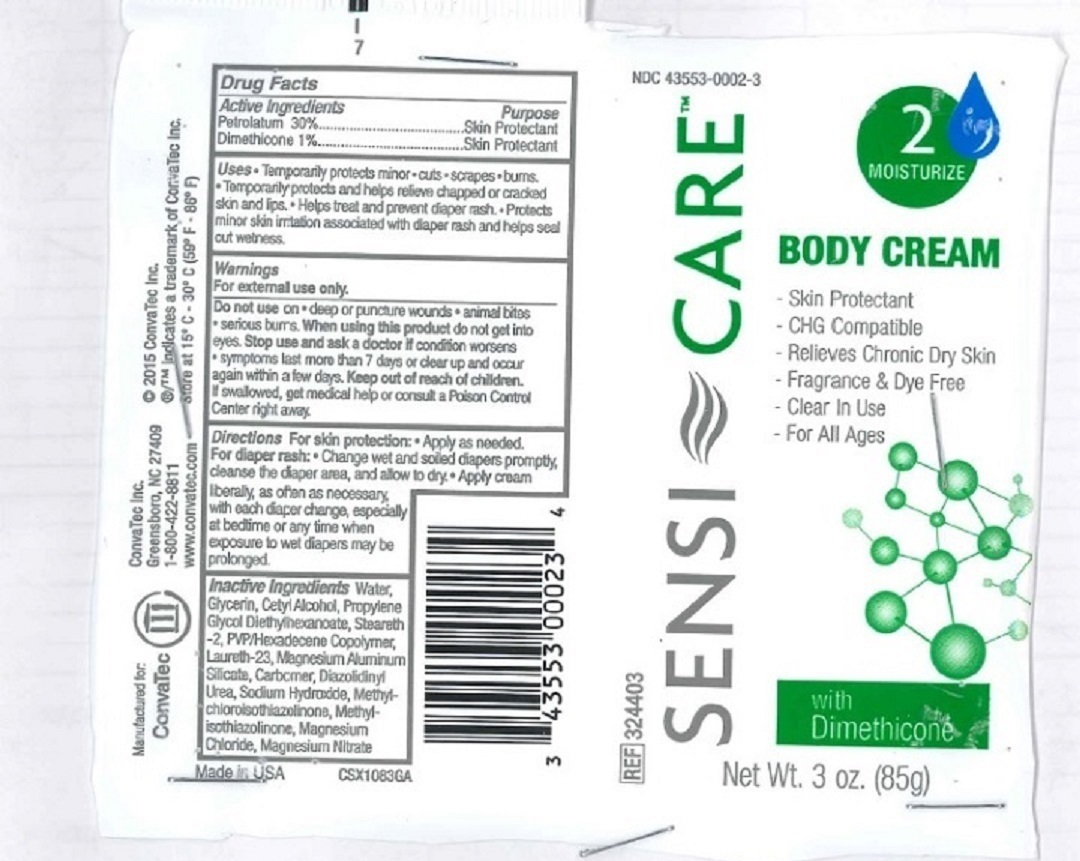 DRUG LABEL: Sensi Care Body Cream
NDC: 11099-0002 | Form: CREAM
Manufacturer: Guest Packaging LLC.
Category: otc | Type: HUMAN OTC DRUG LABEL
Date: 20160618

ACTIVE INGREDIENTS: PETROLATUM 25.5 g/85 g; DIMETHICONE 850 mg/85 g
INACTIVE INGREDIENTS: WATER; GLYCERIN; CETYL ALCOHOL; PROPYLENE GLYCOL DIETHYLHEXANOATE; STEARETH-2; VINYLPYRROLIDONE/HEXADECENE COPOLYMER; LAURETH-23; MAGNESIUM ALUMINUM SILICATE; CARBOMER HOMOPOLYMER TYPE B (ALLYL SUCROSE CROSSLINKED); DIAZOLIDINYL UREA; SODIUM HYDROXIDE; METHYLCHLOROISOTHIAZOLINONE; METHYLISOTHIAZOLINONE; MAGNESIUM CHLORIDE; MAGNESIUM NITRATE

Sensi CareTM Body Cream

Uses

- Temporarily protects • minor • cuts • scrapes • burns.
- Temporarily protects and helps relieve chapped or cracked skin and lips.
- Helps treat and prevent diaper rash.
- Protects minor skin irritation associated with diaper rash and helps seal out wetness.

Warnings

For external use only.
Do not use on • deep or puncture wounds • animal bites • serious burns.
When using this product do not get into eyes.
Stop use and ask a doctor if condition worsens • symptoms last more than 7 days or clear up and occur again within a few days.

Keep out of reach of children.If swallowed, get medical help or consult a Poison Control Center right away.

Directions

For skin protection: • Apply as needed.
For diaper rash: • Change wet and soiled diapers promptly, cleanse the diaper area, and allow to dry.
• Apply cream liberally, as often as necessary, with each diaper change, especially at bedtime or any time when exposure to wet diapers may be prolonged.

Active ingredients

Petrolatum 30%

Dimethicone 1%

Purpose

Skin Protectant

Inactive ingredients

Water, Glycerin, Cetyl Alcohol, Propylene Glycol Diethylhexanoate, Steareth-2, PVP/Hexadecene Copolymer, Laureth-23, Magnesium Aluminum Silicate, Carbomer, Diazolidinyl Urea, Sodium Hydroxide, Methyl chloroisothiazolinone, Methyl isothiazolinone, Magnesium Chloride, Magnesium Nitrate

Other information Store at 15°C -30°C (59°F - 86°F)

SENSI-CARE TM

BODY CREAM

- Skin Protectant

- CHG Compatible

- Relieves Chronic Dry Skin

- Fragrance & Dye Free

- Clear In Use

- For All Ages

Manufactured for:
ConvaTec

ConvaTec Inc.
Greensboro, NC 27409
1-800-422-8811
www.convatec.com

Made in USA